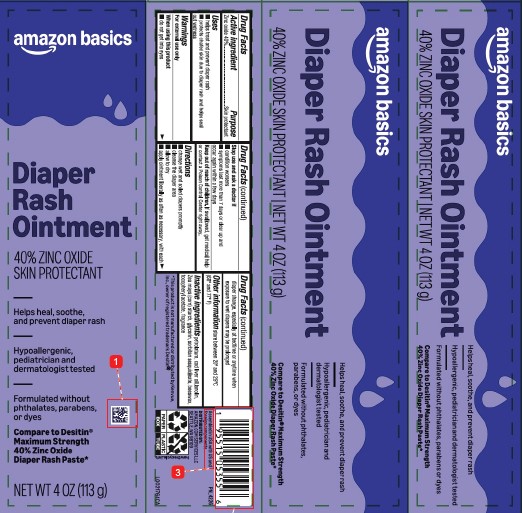 DRUG LABEL: Zinc Oxide
NDC: 72288-989 | Form: OINTMENT
Manufacturer: Amazon.com Services LLC
Category: otc | Type: HUMAN OTC DRUG LABEL
Date: 20260127

ACTIVE INGREDIENTS: ZINC OXIDE 400 mg/1 g
INACTIVE INGREDIENTS: PETROLATUM; COD LIVER OIL; STARCH, CORN; GLYCERIN; SORBITAN SESQUIOLEATE; YELLOW WAX; LANOLIN; .ALPHA.-TOCOPHEROL ACETATE

Basics 020.002/020AD
Diaper Rash Ointment 40% Zinc Oxide

Active ingredient

Zinc oxide 40%

Purpose

Skin protectant

Uses

- helps treat and prevent diaper rash
- protects chafed skin due to diaper rash and helps seal out wetness

Warnings

For external use only

When using this product

- do not get into eyes

Stop use and ask a doctor if

- condition worsens
- symptoms last more than 7 days or clear up and occur again within a few days

Keep out of reach of children.

If swallowed, get medical help or contact a Poison Control Center right away.

Directions

- change wet and soiled diapers promptly
- cleanse the diaper area
- allow to dry
- apply ointment liberally as often as necessary, with each diaper change, especially at bedtime or anytime when exposure to wet diapers may be prolonged

Other information

store between 20º and 25ºC (68º and 77º F)

Inactive ingredients

petrolatum, cod liver oil, lanolin, Zea mays (corn) starch, glycerin, sorbitan sesquioleate, beeswax, tocopheryl acetate, fragrance

Disclaimer

*This product is not manufactured or distributed by Kenvue, Inc., distributor of Desitin®.

Adverse Reactions

Assembled in USA with US and foreign components.

DISTRIBUTED BY: AMAZON.COM SERVICES LLC

SEATTLE, WA 98109

PAPER BOX

PLASTIC TUBE

how2recycle.info

Principal Display Panel

amazon basics

Diaper Rash Ointment

Helps heal, soothe, and prevent diaper rash

Hypoallergenic, pediatrician and dermatologist tested

Formulated without phthalates, parabens, or dyes

Compare to Desitin® Maximum Strength 40% Zinc Oxide Diaper Rash Paste*

40% ZINC OXIDE SKIN PROTECTANT

NET WT 4 OZ (113 g)